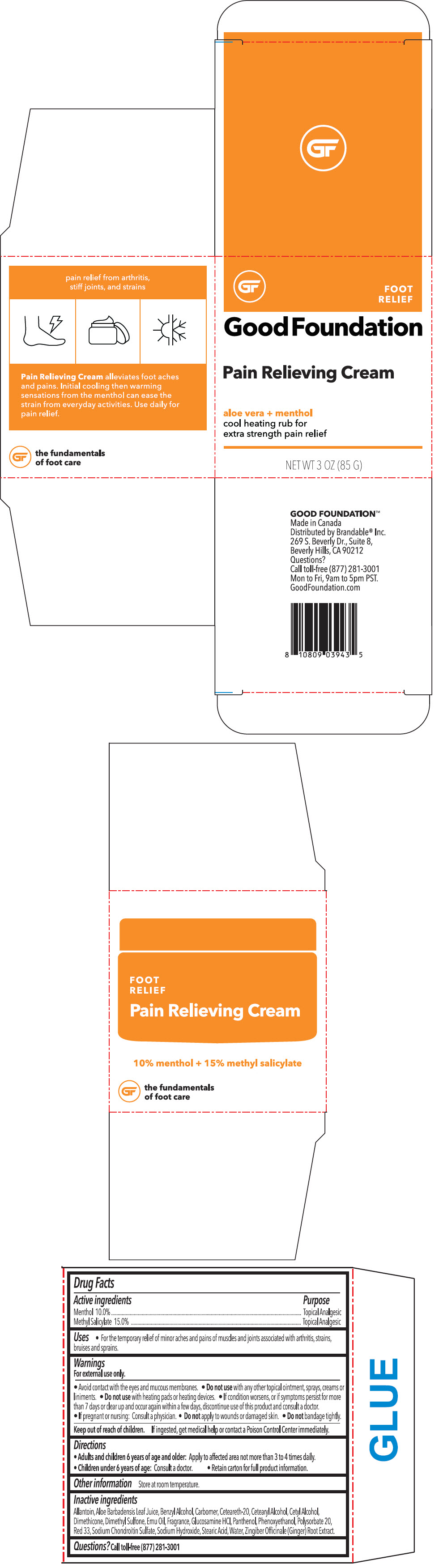 DRUG LABEL: Pain Relieving Foot
NDC: 72764-004 | Form: CREAM
Manufacturer: Brandable
Category: otc | Type: HUMAN OTC DRUG LABEL
Date: 20200224

ACTIVE INGREDIENTS: MENTHYL SALICYLATE, (+/-)- 750 mg/5 g; MENTHOL, UNSPECIFIED FORM 500 mg/5 g
INACTIVE INGREDIENTS: Water; POLYOXYL 20 CETOSTEARYL ETHER; CETOSTEARYL ALCOHOL; Stearic Acid; Cetyl Alcohol; Emu Oil; Dimethyl Sulfone; Dimethicone; ALOE VERA LEAF; Allantoin; SODIUM CHONDROITIN SULFATE (PORCINE; 5500 MW); GLUCOSAMINE HYDROCHLORIDE; GINGER; Panthenol; Polysorbate 20; CARBOXYPOLYMETHYLENE; D&C RED NO. 33; Phenoxyethanol; Benzyl Alcohol; Sodium Hydroxide

Pain Relieving Foot Cream

Drug Facts

ACTIVE INGREDIENT

Active ingredients | Purpose
Menthol 10.0% | Topical Analgesic
Methyl Salicylate 15.0% | Topical Analgesic

Uses

- For the temporary relief of minor aches and pains of muscles and joints associated with arthritis, strains, bruises and sprains.

Warnings

For external use only.

- Avoid contact with the eyes and mucous membranes.

- Do not use with any other topical ointment, sprays, creams or liniments.
- Do not use with heating pads or heating devices.

STOP USE

- If condition worsens, or if symptoms persist for more than 7 days or clear up and occur again within a few days, discontinue use of this product and consult a doctor.

PREGNANCY OR BREAST FEEDING

- If pregnant or nursing: Consult a physician.

- Do not apply to wounds or damaged skin.
- Do not bandage tightly.

Keep out of reach of children. If ingested, get medical help or contact a Poison Control Center immediately.

Directions

- Adults and children 6 years of age and older: Apply to affected area not more than 3 to 4 times daily.
- Children under 6 years of age: Consult a doctor.
- Retain carton for full product information.

Other information

Store at room temperature.

Inactive ingredients

Allantoin, Aloe Barbadensis Leaf Juice, Benzyl Alcohol, Carbomer, Ceteareth-20, Cetearyl Alcohol, Cetyl Alcohol, Dimethicone, Dimethyl Sulfone, Emu Oil, Fragrance, Glucosamine HCl, Panthenol, Phenoxyethanol, Polysorbate 20, Red 33, Sodium Chondroitin Sulfate, Sodium Hydroxide, Stearic Acid, Water, Zingiber Officinale (Ginger) Root Extract.

Questions?

Call toll-free (877) 281-3001

Distributed by Brandable® Inc.
269 S. Beverly Dr., Suite 8,
Beverly Hills, CA 90212

PRINCIPAL DISPLAY PANEL - 85 G Container Box

FOOT
RELIEF

Good Foundation

Pain Relieving Cream

aloe vera + menthol
cool heating rub for
extra strength pain relief

NET WT 3 OZ (85 G)